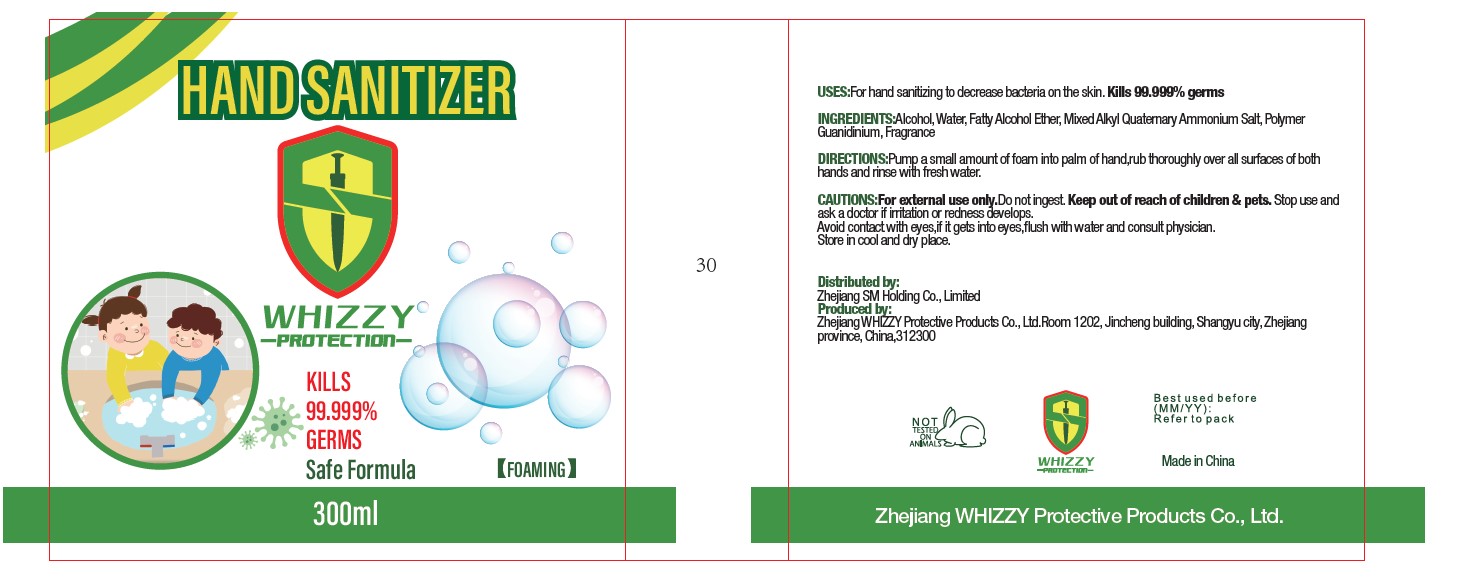 DRUG LABEL: HAND SANITIZER
NDC: 79094-001 | Form: LIQUID
Manufacturer: Zhejiang WHIZZY Protective Products Co.,Ltd
Category: otc | Type: HUMAN OTC DRUG LABEL
Date: 20200618

ACTIVE INGREDIENTS: ALCOHOL 5 mL/100 mL
INACTIVE INGREDIENTS: LINALOOL, (+/-)-; DIPROPYLENE GLYCOL; C10-16 PARETH-1; HEXAMETHYLINDANOPYRAN; PHENYLETHYL ALCOHOL; METHYL DIHYDROJASMONATE (SYNTHETIC); GERANIOL; .BETA.-CITRONELLOL, (+/-)-; DILAURYLDIMONIUM CHLORIDE; DIMYRISTYLDIMONIUM CHLORIDE; WATER

hand sanitizer

Active Ingredient(s)

Alcohol 5% v/v,Didodecyldimethylammonium Chloride 0.25% v/v,dimethylditetradecylammonium chloride 0.15% v/v

Purpose

Antiseptic, Hand Sanitizer

Use

For Hand Sanitizing to decrease bacteria on the skin.kills 99.999%germs

Warnings

For external use only.do not ingest. Keep out of reach of children & pets.stop use ans ask a doctor if irritation or redness develops. avoid contact with eyes if it gets inti eyes flush with water and consult physician

Do not use

- in children less than 2 months of age
- on open skin wounds

Stop use and ask a doctor if irritation or redness develops.

avoid contact with eyes,if it gets into eyes,flush with water and consult physician

Stop use and ask a doctor if irritation or rash occurs. These may be signs of a serious condition.

Keep out of reach of children & pets

Directions

pump a small amount of foam into palm of hand,rub thoroughly over all surfaces of both hands and rinse with fresh water

Other information

Store in cool and dry place

Inactive ingredients

water,fatty alcohol ether, Mixed alkyl quaternary ammounium salt ,polumer guanidinium,fragrance